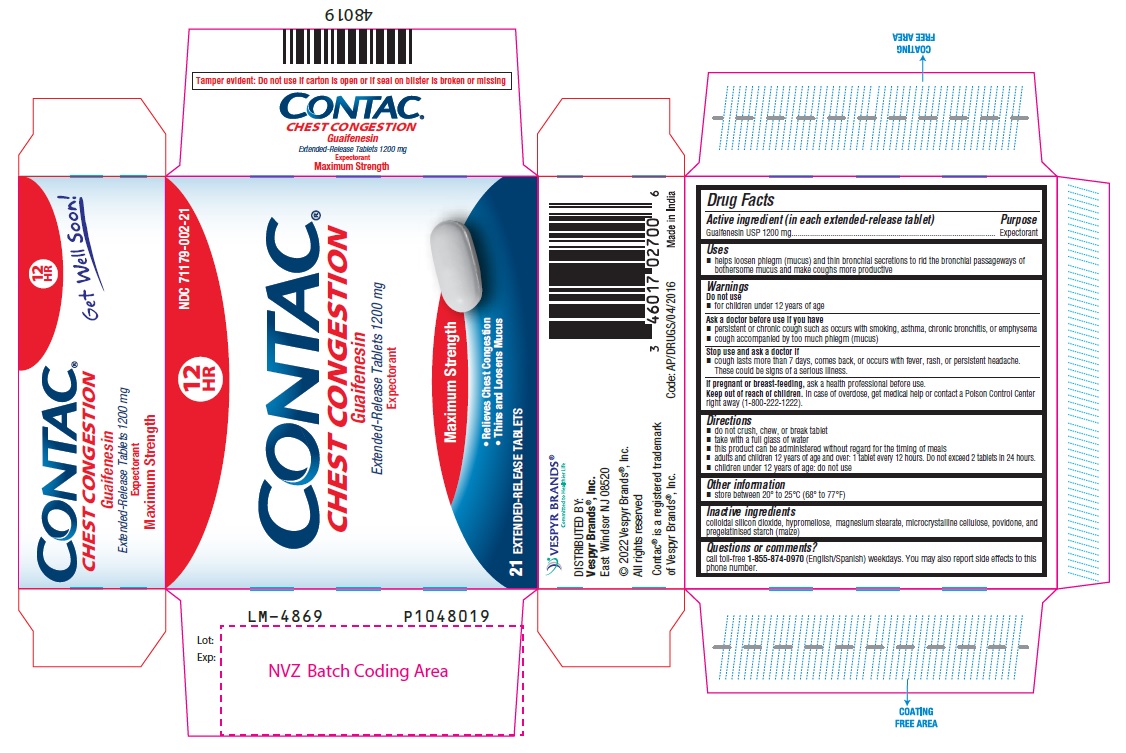 DRUG LABEL: Guaifenesin
NDC: 71179-002 | Form: TABLET, EXTENDED RELEASE
Manufacturer: VESPYR BRANDS, INC.
Category: otc | Type: Human OTC Drug Label
Date: 20231201

ACTIVE INGREDIENTS: GUAIFENESIN 1200 mg/1 1
INACTIVE INGREDIENTS: SILICON DIOXIDE; HYPROMELLOSE 2208 (15000 MPA.S); HYPROMELLOSE 2910 (10000 MPA.S); MAGNESIUM STEARATE; MICROCRYSTALLINE CELLULOSE 101; MICROCRYSTALLINE CELLULOSE 102; POVIDONE K90; POVIDONE K25; STARCH, CORN

Drug Facts

Active ingredient

(in each extended-release tablet)
Guaifenesin USP 1200 mg

Purpose

Expectorant

Uses

- helps loosen phlegm (mucus) and thin bronchial secretions to rid the bronchial passageways of bothersome mucus and make coughs more productive

Warnings

Do not use

- for children under 12 years of age

Ask a doctor before use if you have

- persistent or chronic cough such as occurs with smoking, asthma, chronic bronchitis, or emphysema
- cough accompanied by too much phlegm (mucus)

Stop use and ask a doctor if

- cough lasts more than 7 days, comes back, or occurs with fever, rash, or persistent headache. These could be signs of a serious illness.

If pregnant or breast-feeding,

ask a health professional before use.

Keep out of reach of children.

In case of overdose, get medical help or contact a Poison Control Center right away (1-800-222-1222).

Directions

- do not crush, chew, or break tablet
- take with a full glass of water
- this product can be administered without regard for the timing of meals
- adults and children 12 years of age and over: 1 tablet every 12 hours. Do not exceed 2 tablets in 24 hours.
- children under 12 years of age: do not use

Other information

- store between 20° to 25°C (68° to 77°F)

Inactive ingredients

colloidal silicon dioxide, hypromellose, magnesium stearate, microcrystalline cellulose, povidone, and pregelatinised starch (maize)

Questions or comments?

call toll-free 1-855-874-0970 (English/Spanish) weekdays. You may also report side effects to this phone number.

DISTRIBUTED BY:
Vespyr Brands®, Inc.
East Windsor, NJ 08520
Made in India
Code: AP/DRUGS/04/2016

PACKAGE LABEL-PRINCIPAL DISPLAY PANEL - 1200 mg Blister Carton (21 Tablets)

12 NDC 71179-002-21
HR
CONTAC®
CHEST CONGESTION
Guaifenesin
Extended-Release Tablets 1200 mg
Expectorant
Maximum Strength

- Relieves Chest Congestion
- Thins And Loosens Mucus

21 EXTENDED-RELEASE TABLETS